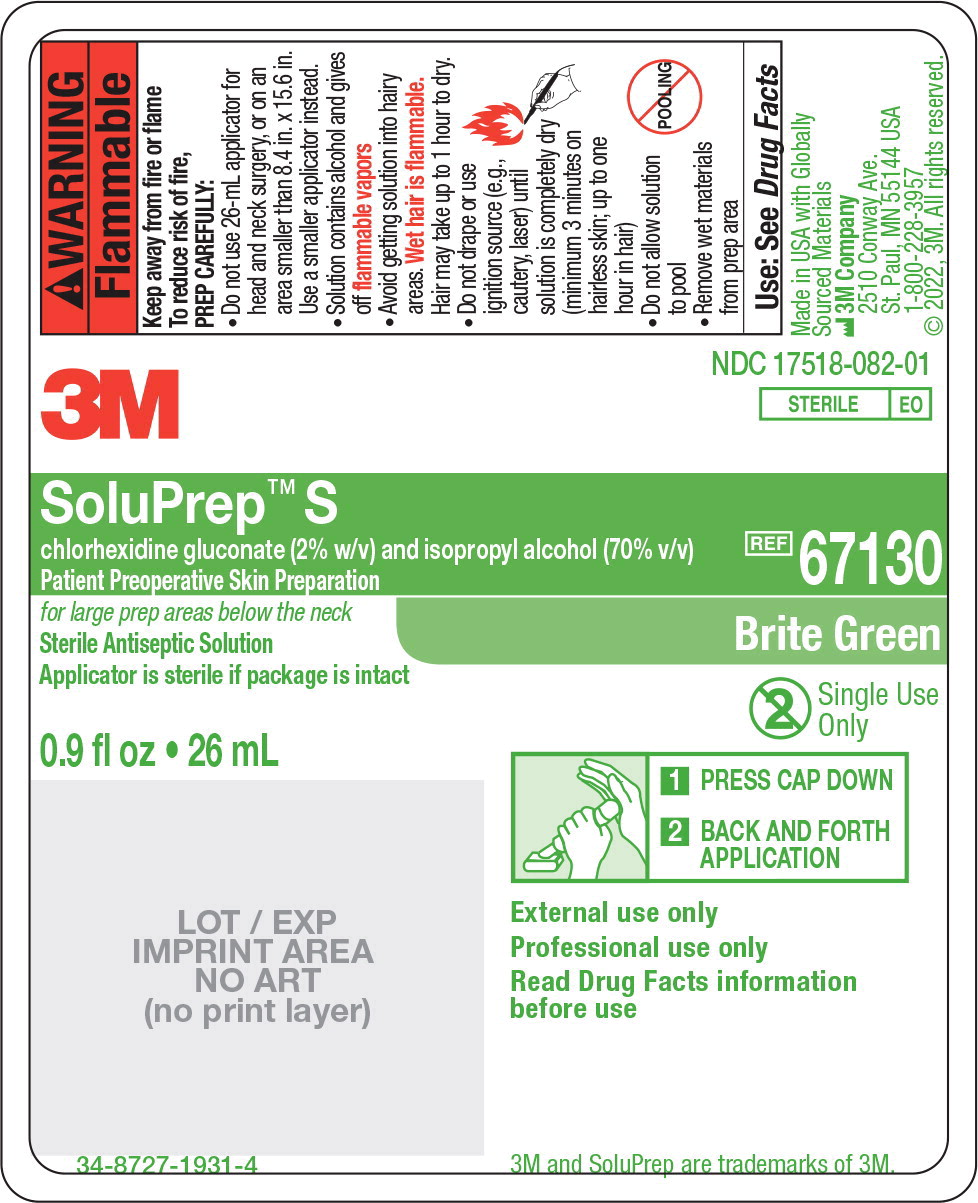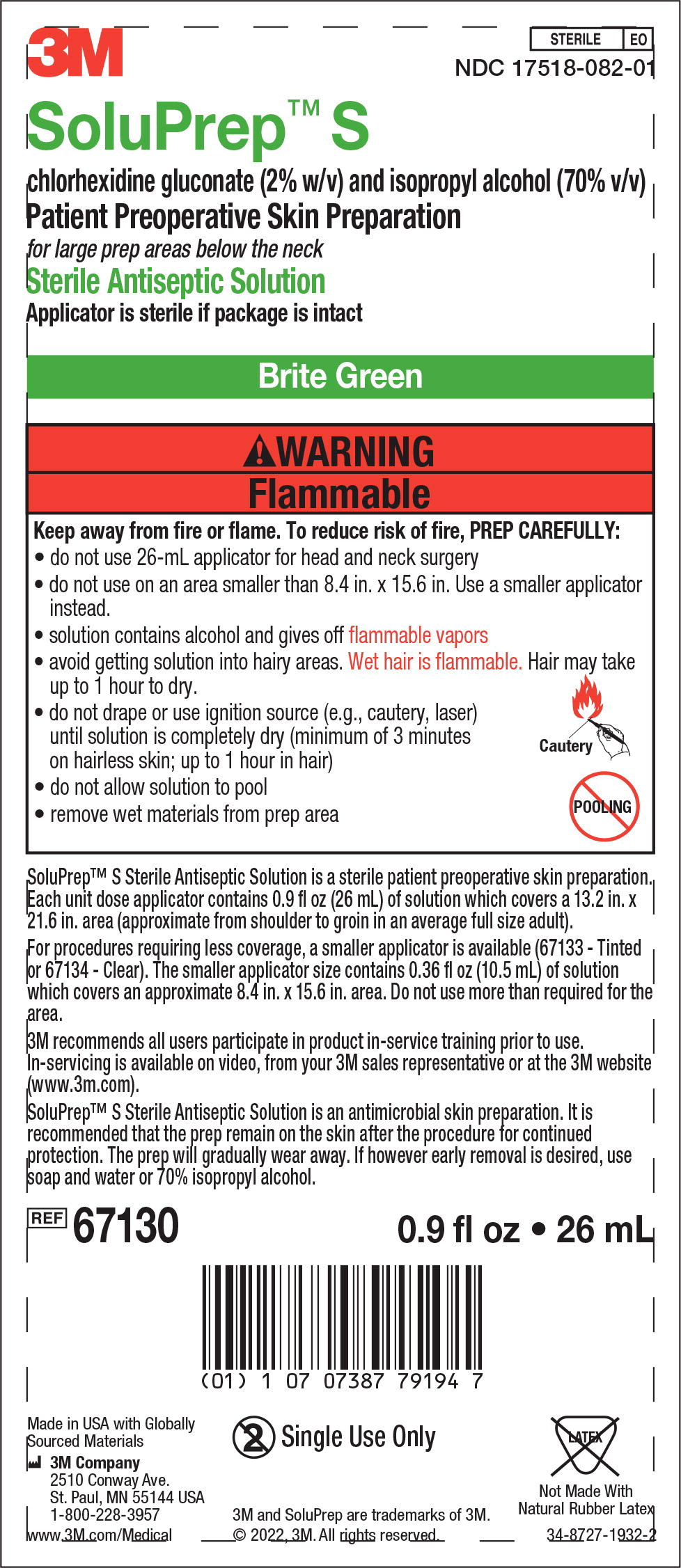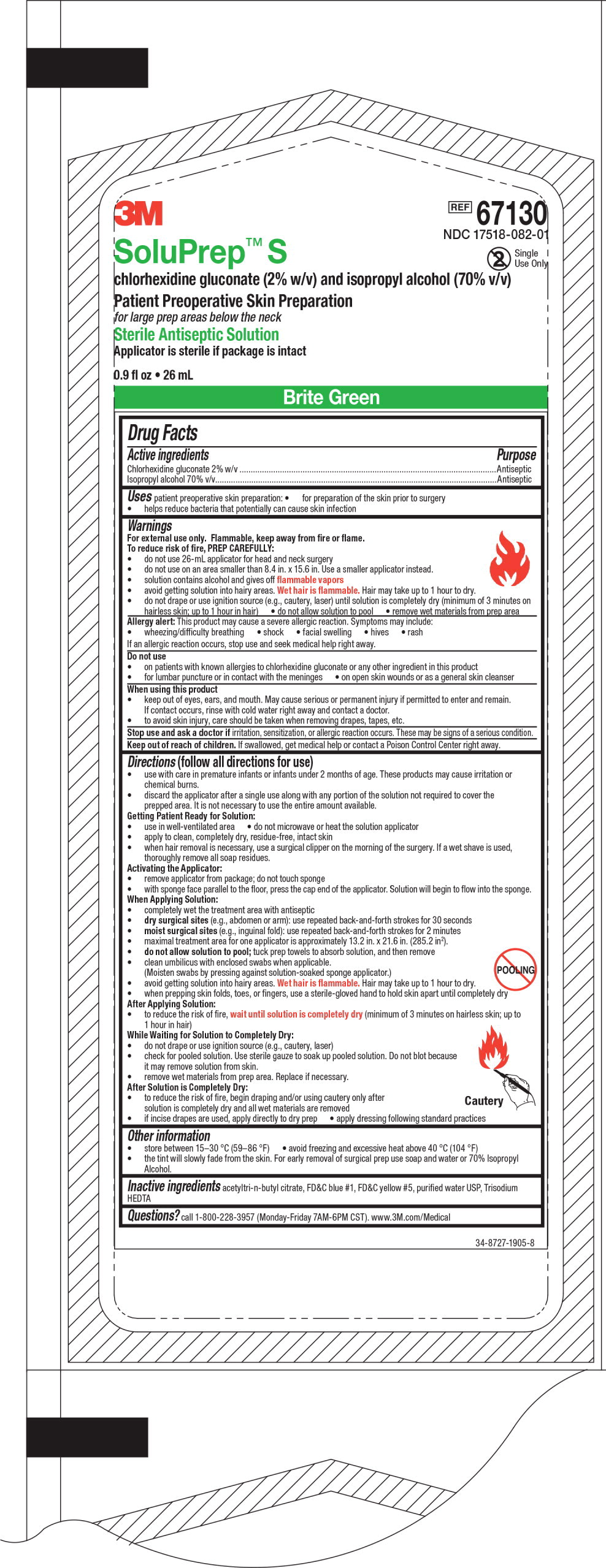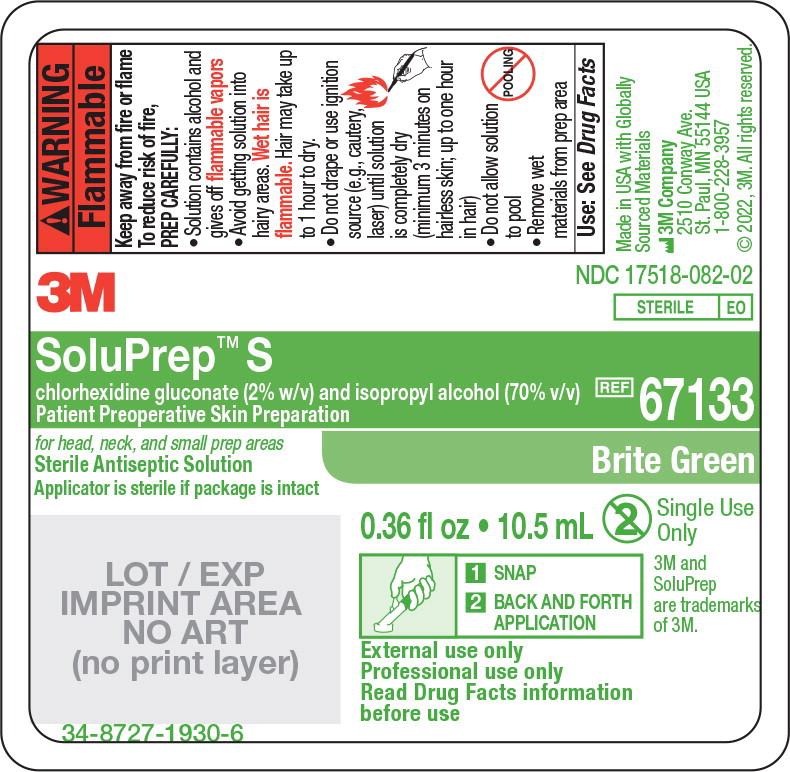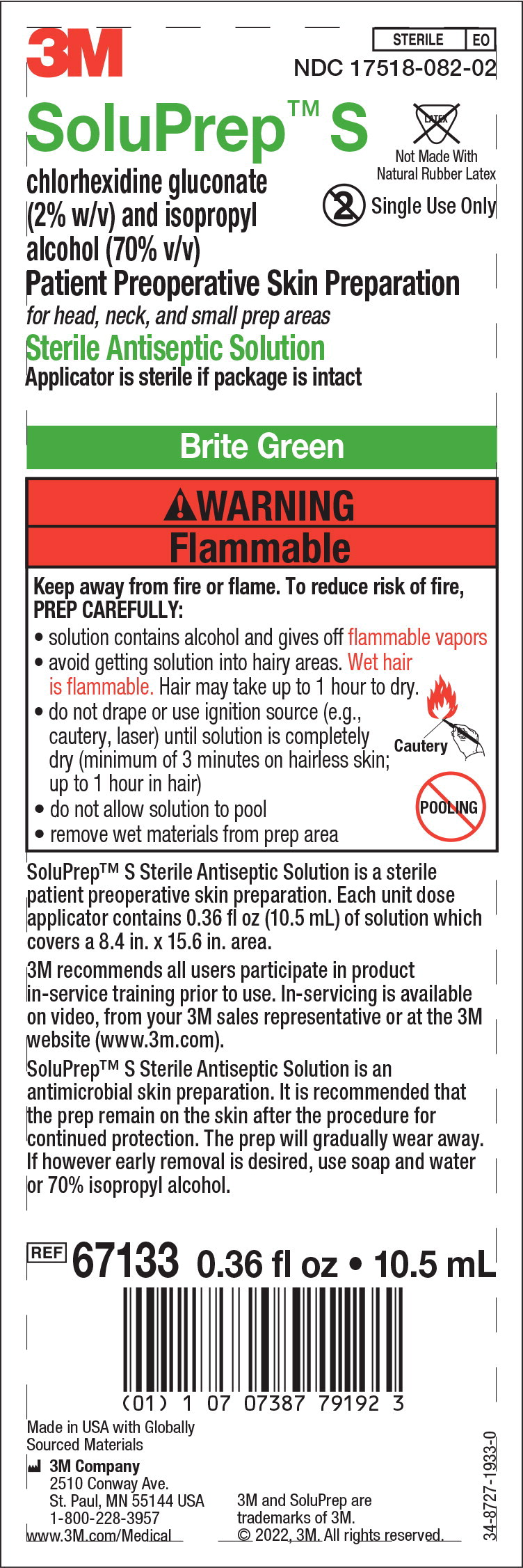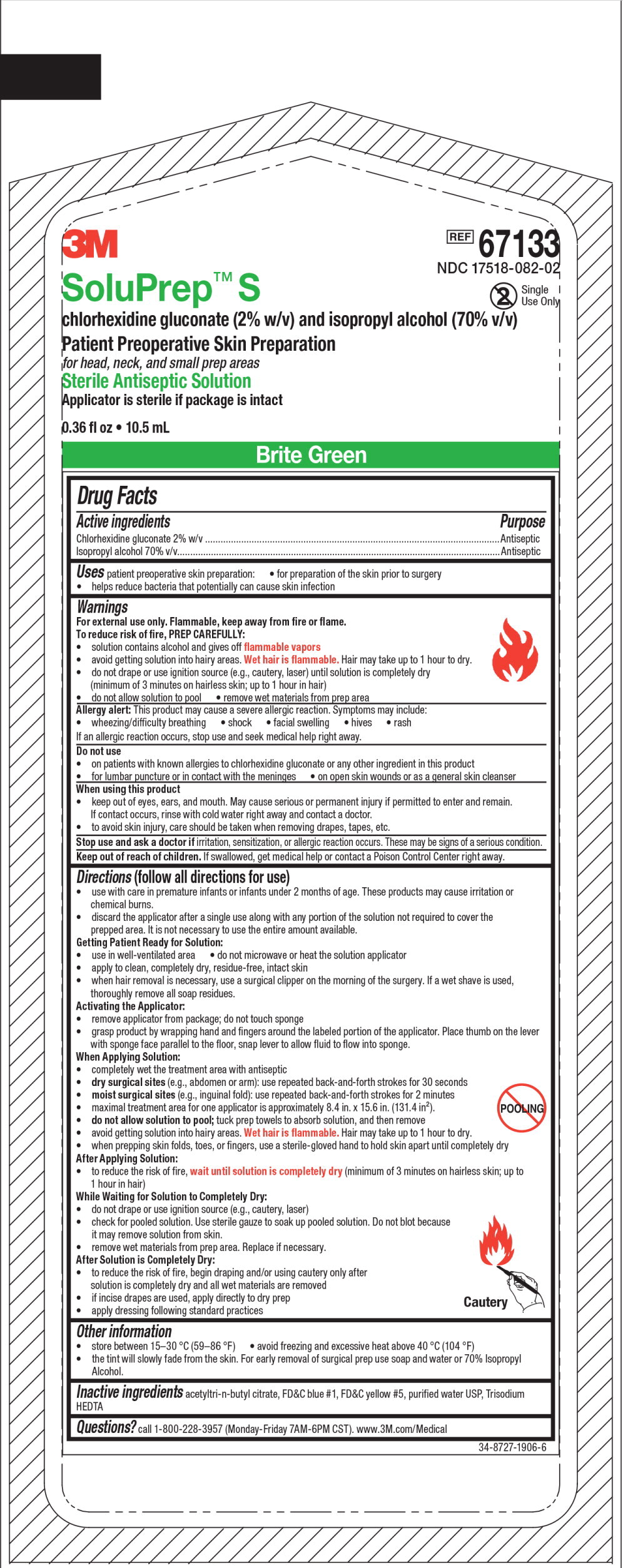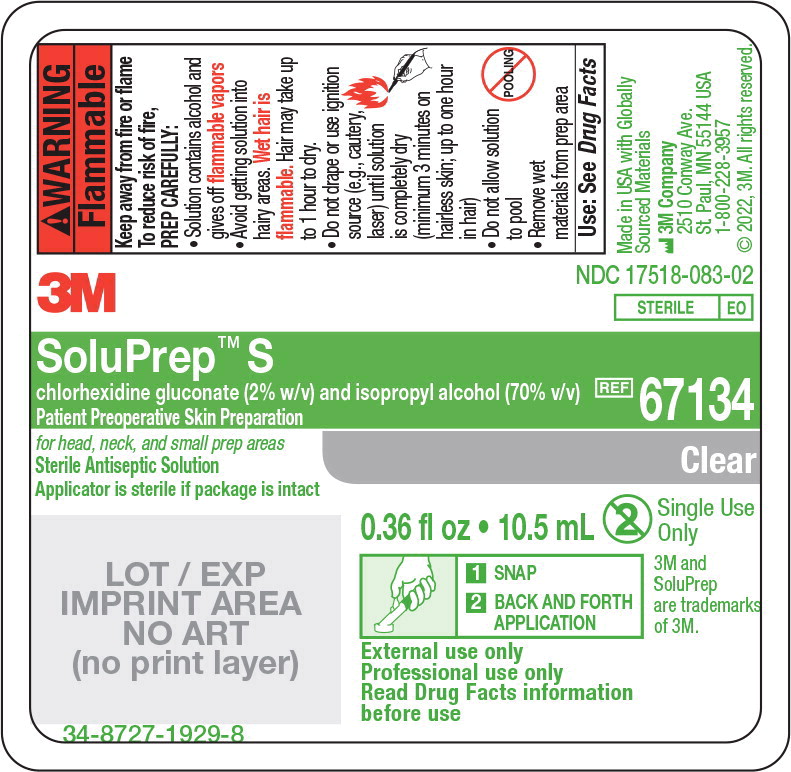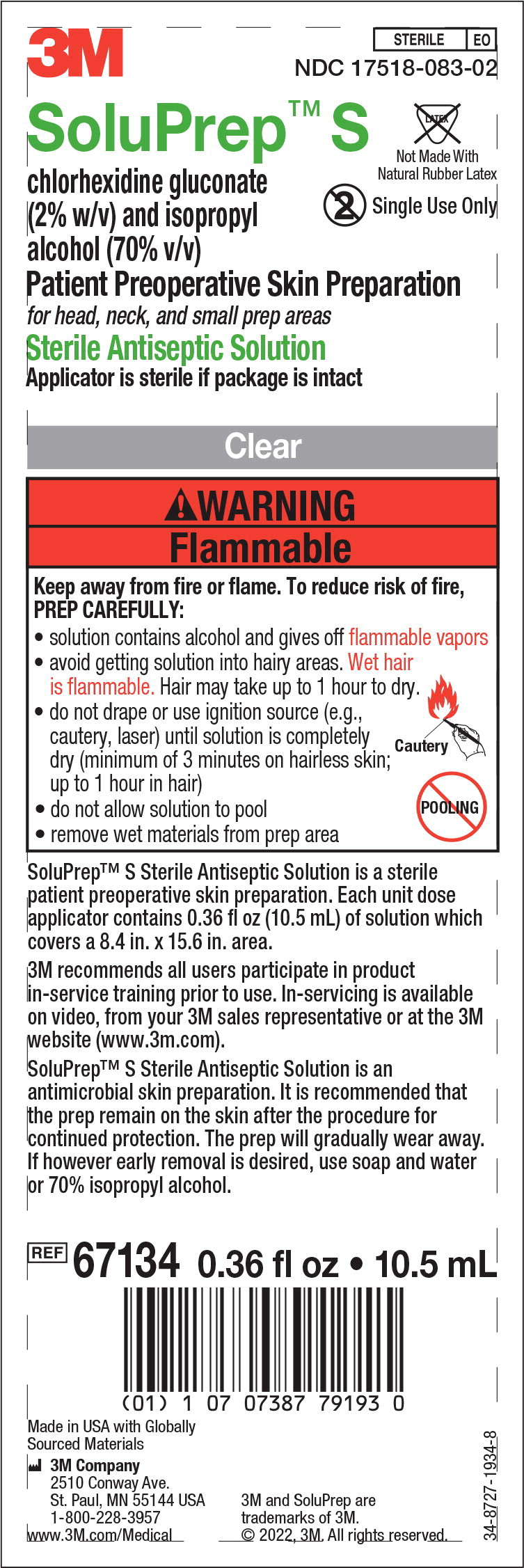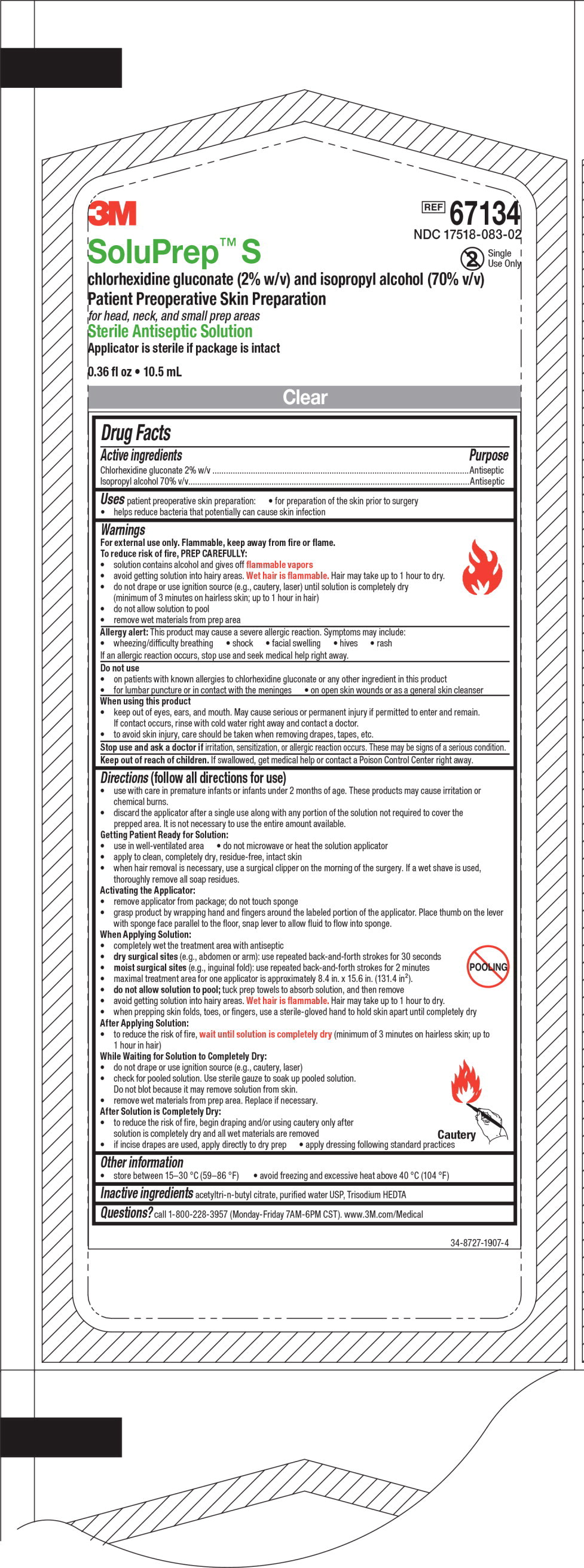 DRUG LABEL: 3M SoluPrep S
NDC: 17518-082 | Form: SOLUTION
Manufacturer: Solventum US LLC
Category: otc | Type: HUMAN OTC DRUG LABEL
Date: 20240801

ACTIVE INGREDIENTS: Chlorhexidine Gluconate 20 mg/1 mL; Isopropyl Alcohol 0.7 mL/1 mL
INACTIVE INGREDIENTS: Acetyltributyl Citrate; FD&C BLUE NO. 1; FD&C YELLOW NO. 5; Water; Trisodium Hedta

3M SoluPrep™ S 26mL Brite Green Applicator

Drug Facts

Active ingredients

Chlorhexidine gluconate 2% w/v

Isopropyl alcohol 70% v/v

Purpose

Antiseptic

Antiseptic

Uses

patient preoperative skin preparation:

- for preparation of the skin prior to surgery
- helps reduce bacteria that potentially can cause skin infection

Warnings

For external use only. Flammable, keep away from fire or flame.

To reduce risk of fire, PREP CAREFULLY:

- do not use 26-mL applicator for head and neck surgery
- do not use on an area smaller than 8.4 in. x 15.6 in. Use a smaller applicator instead.
- solution contains alcohol and gives off flammable vapors
- avoid getting solution into hairy areas. Wet hair is flammable. Hair may take up to 1 hour to dry.
- do not drape or use ignition source (e.g., cautery, laser) until solution is completely dry (minimum of 3 minutes on hairless skin; up to 1 hour in hair)
- do not allow solution to pool
- remove wet materials from prep area

Allergy Alert: This product may cause a severe allergic reaction. Symptoms may include:

- wheezing/difficulty breathing
- shock
- facial swelling
- hives
- rash

If an allergic reaction occurs, stop use and seek medical help right away.

Do not use

- on patients with known allergies to chlorhexidine gluconate or any other ingredient in this product
- for lumbar puncture or in contact with the meninges
- on open skin wounds or as a general skin cleanser

When using this product

- keep out of eyes, ears, and mouth. May cause serious or permanent injury if permitted to enter and remain. If contact occurs, rinse with cold water right away and contact a doctor.
- to avoid skin injury, care should be taken when removing drapes, tapes, etc.

Stop use and ask a doctor if irritation, sensitization, or allergic reaction occurs. These may be signs of a serious condition.

Keep out of reach of children. If swallowed, get medical help or contact a Poison Control Center right away.

Directions (follow all directions for use)

- use with care in premature infants or infants under 2 months of age. These products may cause irritation or chemical burns.
- discard the applicator after a single use along with any portion of the solution not required to cover the prepped area. It is not necessary to use the entire amount available.

Getting Patient Ready for Solution:

- use in well-ventilated area
- do not microwave or heat the solution applicator
- apply to clean, completely dry, residue-free, intact skin
- when hair removal is necessary, use a surgical clipper on the morning of the surgery. If a wet shave is used, thoroughly remove all soap residues.

Activating the Applicator:

- remove applicator from package; do not touch sponge
- with sponge face parallel to the floor, press the cap end of the applicator. Solution will begin to flow into sponge.

When Applying Solution:

- completely wet the treatment area with antiseptic
- dry surgical sites (e.g., abdomen or arm): use repeated back-and-forth strokes for 30 seconds
- moist surgical sites (e.g., inguinal fold): use repeated back-and-forth strokes for 2 minutes
- maximal treatment area for one applicator is approximately 13.2 in. x 21.6 in. (285.2 in^2).
- do not allow solution to pool; tuck prep towels to absorb solution, and then remove
- clean umbilicus with enclosed swabs when applicable.
- (Moisten swabs by pressing against solution-soaked sponge applicator.)
- avoid getting solution into hairy areas. Wet hair is flammable. Hair may take up to 1 hour to dry.
- when prepping skin folds, toes, or fingers, use a sterile-gloved hand to hold skin apart until completely dry.

After Applying Solution:

- to reduce the risk of fire, wait until solution is completely dry (minimum of 3 minutes on hairless skin; up to 1 hour in hair)

While Waiting for Solution to Completely Dry:

- do not drape or use ignition source (e.g., cautery, laser)
- check for pooled solution. Use sterile gauze to soak up pooled solution. Do not blot because it may remove solution from skin.
- remove wet materials from prep area. Replace if necessary.

After Solution is Completely Dry:

- to reduce the risk of fire, begin draping and/or using cautery only after solution is completely dry and all wet materials are removed
- if incise drapes are used, apply directly to dry prep
- apply dressing following standard practices

Other information

- store between 15-30 °C (59-86 °F)
- avoid freezing and excessive heat above 40 °C (104 °F)
- The tint will slowly fade from the skin. For early removal of surgical prep use soap and water or 70% Isopropyl Alcohol.

Inactive ingredients

acetyltri-n-butyl citrate, FD&C blue #1, FD&C yellow #5, purified water USP, Trisodium HEDTA

Questions?

call 1-800-228-3957 (Monday-Friday 7AM-6PM CST). www.3M.com/Medical

34-8727-1905-8

3M SoluPrep™ S 10.5mL Brite Green Applicator

Drug Facts

Active ingredients

Chlorhexidine gluconate 2% w/v

Isopropyl alcohol 70% v/v

Purpose

Antiseptic

Antiseptic

Uses

patient preoperative skin preparation:

- for preparation of the skin prior to surgery
- helps reduce bacteria that potentially can cause skin infection

Warnings

For external use only. Flammable, keep away from fire or flame.

To reduce risk of fire, PREP CAREFULLY:

- solution contains alcohol and gives off flammable vapors
- avoid getting solution into hairy areas. Wet hair is flammable. Hair may take up to 1 hour to dry.
- do not drape or use ignition source (e.g., cautery, laser) until solution is completely dry (minimum of 3 minutes on hairless skin; up to 1 hour in hair)
- do not allow solution to pool
- remove wet materials from prep area

Allergy Alert: This product may cause a severe allergic reaction. Symptoms may include:

- wheezing/difficulty breathing
- shock
- facial swelling
- hives
- rash

If an allergic reaction occurs, stop use and seek medical help right away.

Do not use

- on patients with known allergies to chlorhexidine gluconate or any other ingredient in this product
- for lumbar puncture or in contact with the meninges
- on open skin wounds or as a general skin cleanser

When using this product

- keep out of eyes, ears, and mouth. May cause serious or permanent injury if permitted to enter and remain. If contact occurs, rinse with cold water right away and contact a doctor.
- to avoid skin injury, care should be taken when removing drapes, tapes, etc.

Stop use and ask a doctor if irritation, sensitization, or allergic reaction occurs. These may be signs of a serious condition.

Keep out of reach of children. If swallowed, get medical help or contact a Poison Control Center right away.

Directions (follow all directions for use)

- use with care in premature infants or infants under 2 months of age. These products may cause irritation or chemical burns.
- discard the applicator after a single use along with any portion of the solution not required to cover the prepped area. It is not necessary to use the entire amount available.

Getting Patient Ready for Solution:

- use in well-ventilated area
- do not microwave or heat the solution applicator
- apply to clean, completely dry, residue-free, intact skin
- when hair removal is necessary, use a surgical clipper on the morning of the surgery. If a wet shave is used, thoroughly remove all soap residues.

Activating the Applicator:

- remove applicator from package; do not touch sponge
- grasp products by wrapping hand and fingers around the labeled portion of the applicator. Place thumb on the lever with sponge face parallel to the floor, snap lever to allow fluid to flow into sponge.

When Applying Solution:

- completely wet the treatment area with antiseptic
- dry surgical sites (e.g., abdomen or arm): use repeated back-and-forth strokes for 30 seconds
- moist surgical sites (e.g., inguinal fold): use repeated back-and-forth strokes for 2 minutes
- maximal treatment area for one applicator is approximately 8.4 in. x 15.6 in. (131.4 in^2).
- do not allow solution to pool; tuck prep towels to absorb solution, and then remove
- avoid getting solution into hairy areas. Wet hair is flammable. Hair may take up to 1 hour to dry.
- when prepping skin folds, toes, or fingers, use a sterile-gloved hand to hold skin apart until completely dry.

After Applying Solution:

- to reduce the risk of fire, wait until solution is completely dry (minimum of 3 minutes on hairless skin; up to 1 hour in hair)

While Waiting for Solution to Completely Dry:

- do not drape or use ignition source (e.g., cautery, laser)
- check for pooled solution. Use sterile gauze to soak up pooled solution. Do not blot because it may remove solution from skin.
- remove wet materials from prep area. Replace if necessary.

After Solution is Completely Dry:

- to reduce the risk of fire, begin draping and/or using cautery only after solution is completely dry and all wet materials are removed
- if incise drapes are used, apply directly to dry prep
- apply dressing following standard practices

Other information

- store between 15-30 °C (59-86 °F)
- avoid freezing and excessive heat above 40 °C (104 °F)
- The tint will slowly fade from the skin. For early removal of surgical prep use soap and water or 70% Isopropyl Alcohol.

Inactive ingredients

acetyltri-n-butyl citrate, FD&C blue #1, FD&C yellow #5, purified water USP, Trisodium HEDTA

Questions?

call 1-800-228-3957 (Monday-Friday 7AM-6PM CST). www.3M.com/Medical

34-8727-1906-6

3M SoluPrep™ S 10.5mL Clear Applicator

Drug Facts

Active ingredients

Chlorhexidine gluconate 2% w/v

Isopropyl alcohol 70% v/v

Purpose

Antiseptic

Antiseptic

Uses

patient preoperative skin preparation:

- for preparation of the skin prior to surgery
- helps reduce bacteria that potentially can cause skin infection

Warnings

- For external use only. Flammable, keep away from fire or flame.
- To reduce risk of fire, PREP CAREFULLY:
- solution contains alcohol and gives off flammable vapors
- avoid getting solution into hairy areas. Wet hair is flammable. Hair may take up to 1 hour to dry.
- do not drape or use ignition source (e.g., cautery, laser) until solution is completely dry (minimum of 3 minutes on hairless skin; up to 1 hour in hair)
- do not allow solution to pool
- remove wet materials from prep area

Allergy Alert: This product may cause a severe allergic reaction. Symptoms may include:

- wheezing/difficulty breathing
- shock
- facial swelling
- hives
- rash

If an allergic reaction occurs, stop use and seek medical help right away.

Do not use

- on patients with known allergies to chlorhexidine gluconate or any other ingredient in this product
- for lumbar puncture or in contact with the meninges
- on open skin wounds or as a general skin cleanser

When using this product

- keep out of eyes, ears, and mouth. May cause serious or permanent injury if permitted to enter and remain. If contact occurs, rinse with cold water right away and contact a doctor.
- to avoid skin injury, care should be taken when removing drapes, tapes, etc.

Stop use and ask a doctor if irritation, sensitization, or allergic reaction occurs. These may be signs of a serious condition.

Keep out of reach of children. If swallowed, get medical help or contact a Poison Control Center right away.

Directions (follow all directions for use)

- use with care in premature infants or infants under 2 months of age. These products may cause irritation or chemical burns.
- discard the applicator after a single use along with any portion of the solution not required to cover the prepped area. It is not necessary to use the entire amount available.

Getting Patient Ready for Solution:

- use in well-ventilated area
- do not microwave or heat the solution applicator
- apply to clean, completely dry, residue-free, intact skin
- when hair removal is necessary, use a surgical clipper on the morning of the surgery. If a wet shave is used, thoroughly remove all soap residues.

Activating the Applicator:

- remove applicator from package; do not touch sponge
- grasp product by wrapping hand and fingers around the labeled portion of the applicator. Place thumb on the lever with sponge face parallel to the floor, snap lever to allow fluid to flow into sponge.

When Applying Solution:

- completely wet the treatment area with antiseptic
- dry surgical sites (e.g., abdomen or arm): use repeated back-and-forth strokes for 30 seconds
- moist surgical sites (e.g., inguinal fold): use repeated back-and-forth strokes for 2 minutes
- maximal treatment area for one applicator is approximately 8.4 in. x 15.6 in. (131.4 in^2)
- do not allow solution to pool; tuck prep towels to absorb solution, and then remove
- avoid getting solution into hairy areas. Wet hair is flammable. Hair may take up to 1 hour to dry.
- when prepping skin folds, toes, or fingers, use a sterile-gloved hand to hold skin apart until completely dry.

After Applying Solution:

- to reduce the risk of fire, wait until solution is completely dry (minimum of 3 minutes on hairless skin; up to 1 hour in hair)

While Waiting for Solution to Completely Dry:

- do not drape or use ignition source (e.g., cautery, laser)
- check for pooled solution. Use sterile gauze to soak up pooled solution. Do not blot because it may remove solution from skin.
- remove wet materials from prep area. Replace if necessary.

After Solution is Completely Dry:

- to reduce the risk of fire, begin draping and/or using cautery only after solution is completely dry and all wet materials are removed
- if incise drapes are used, apply directly to dry prep
- apply dressing following standard practices

Other information

- store between 15-30 °C (59-86 °F)
- avoid freezing and excessive heat above 40 °C (104 °F)

Inactive ingredients

acetyltri-n-butyl citrate, purified water USP, Trisodium HEDTA

Questions?

call 1-800-228-3957 (Monday-Friday 7AM-6PM CST). www.3M.com/Medical

34-8727-1907-4

Principal Display Panel - 26mL Brite Green Applicator Label

3M

NDC 17518-082-01

STERILE EO

SoluPrep™ S

chlorhexidine gluconate (2% w/v) and isopropyl alcohol (70% v/v)

Patient Preoperative Skin Preparation

REF 67130

for large prep areas below the neck

Sterile Antiseptic Solution

Applicator is sterile if package is intact

Brite Green

0.9 fl oz • 26 mL

Single Use

Only

PRESS CAP DOWN

BACK AND FORTH

APPLICATION

External use only

Professional use only

Read Drug Facts information

before use

34-8727-1931-4

3M and SoluPrep are trademarks of 3M.

Principal Display Panel - 26mL Brite Green Applicator Insert Label

3M

STERILE EO

NDC 17518-082-01

SoluPrep™ S

chlorhexidine gluconate (2% w/v) and isopropyl alcohol (70% v/v)

Patient Preoperative Skin Preparation

for large prep areas below the neck

Sterile Antiseptic Solution

Applicator is sterile if package is intact

Brite Green

SoluPrep™ S Sterile Antiseptic Solution is a sterile patient preoperative skin preparation.

Each unit dose applicator contains 0.9 fl oz (26 mL) of solution which covers a 13.2 in. x 21.6 in. area (approximate from shoulder to groin in an average full size adult).

For procedures requiring less coverage, a smaller applicator is available (67133 - Tinted or

67134 - Clear). The smaller applicator size contains 0.36 fl oz (10.5 mL) of solution which

covers an approximate 8.4 in. x 15.6 in. area. Do not use more than required for the area.

3M recommends all users participate in product in-service training prior to use.

In-servicing is available on video, from your 3M sales representative or at the 3M website

(www.3m.com).

SoluPrep™ S Sterile Antiseptic Solution is an antimicrobial skin preparation. It is

recommended that the prep remain on the skin after the procedure for continued

protection. The prep will gradually wear away. If however early removal is desired, use

soap and water or 70% isopropyl alcohol.

REF 67130

0.9 fl oz • 26 mL

Made in USA with Globally

Sourced Materials

3M Company

2510 Conway Ave.

St. Paul, MN 55144 USA

1-800-228-3957

www.3M.com/Medical

Single Use Only

3M and SoluPrep are trademarks of 3M.

@ 2022, 3M. All rights reserved.

Not Made With

Natural Rubber Latex

34-8727-1932-2

Principal Display Panel – 3M SoluPrep™ S 26mL Brite Green Applicator Pouch Label

3M

REF 67130

NDC 17518-082-01

Single

Use Only

SoluPrep™ S

chlorhexidine gluconate (2% w/v) and isopropyl alcohol (70% v/v)

Patient Preoperative Skin Preparation

for large prep areas below the neck

Sterile Antiseptic Solution

Applicator is sterile if package is intact

0.9 fl oz • 26 mL

Brite Green

Principal Display Panel – 10.5mL Brite Green Applicator Label

3M

NDC 17518-082-02

STERILE EO

SoluPrep™ S

chlorhexidine gluconate (2% w/v) and isopropyl alcohol (70% v/v)

Patient Preoperative Skin Preparation

REF 67133

for head, neck, and small prep areas

Sterile Antiseptic Solution

Applicator is sterile if package is intact

Brite Green

0.36 fl oz • 10.5 mL

Single Use

Only

3M and

SoluPrep

are trademarks

of 3M.

SNAP

BACK AND FORTH

APPLICATION

External use only

Professional use only

Read Drug Facts information

before use

34-8727-1930-6

Principal Display Panel – 10.5mL Brite Green Applicator Insert Label

3M

STERILE EO

NDC 17518-082-02

SoluPrep™ S

chlorhexidine gluconate

(2% w/v) and isopropyl

alcohol (70% v/v)

Patient Preoperative Skin Preparation

for head, neck, and small prep areas

Sterile Antiseptic Solution

Applicator is sterile if package is intact

Brite Green

SoluPrep™ S Sterile Antiseptic Solution is a sterile

patient preoperative skin preparation. Each unit dose

applicator contains 0.36 fl oz (10.5 mL) of solution which

covers a 8.4 in. x 15.6 in. area.

3M recommends all users participate in product

in-service training prior to use. In-servicing is available

on video, from your 3M sales representative or at the 3M

website (www.3m.com).

SoluPrep™ S Sterile Antiseptic Solution is an

antimicrobial skin preparation. It is recommended that

the prep remain on the skin after the procedure for

continued protection. The prep will gradually wear away.

If however early removal is desired, use soap and water

or 70% isopropyl alcohol.

REF 67133

0.36 fl oz • 10.5 mL

Made in USA with Globally

Sourced Materials

3M Company

2510 Conway Ave.

St. Paul, MN 55144 USA

1-800-228-3957

www.3M.com/Medical

3M and SoluPrep are

trademarks of 3M.

@ 2022, 3M. All rights reserved.

34-8727-1933-0

Principal Display Panel – 3M SoluPrep™ S 10.5mL Brite Green Applicator Pouch Label

3M

REF 67133

NDC 17518-082-02

Single

Use Only

SoluPrep™ S

chlorhexidine gluconate (2% w/v) and isopropyl alcohol (70% v/v)

Patient Preoperative Skin Preparation

for head, neck, and small prep areas

Sterile Antiseptic Solution

Applicator is sterile if package is intact

0.36 fl oz • 10.5 mL

Brite Green

Principal Display Panel – 10.5 mL Clear Applicator Label

3M

NDC 17518-083-02

STERILE EO

SoluPrep™ S

chlorhexidine gluconate (2% w/v) and isopropyl alcohol (70% v/v)

Patient Preoperative Skin Preparation

REF 67134

for head, neck, and small prep areas

Sterile Antiseptic Solution

Applicator is sterile if package is intact

Clear

0.36 fl oz • 10.5 mL

SNAP

BACK AND FORTH

APPLICATION

External use only

Professional use only

Read Drug Facts information

before use

Single Use

Only

3M and

SoluPrep

are trademarks

of 3M.

34-8727-1929-8

Principal Display Panel – 10.5mL Clear Insert Label

3M

STERILE EO

NDC 17518-083-02

SoluPrep™ S

chlorhexidine gluconate

(2% w/v) and isopropyl

alcohol (70% v/v)

Patient Preoperative Skin Preparation

for head, neck, and small prep areas

Sterile Antiseptic Solution

Applicator is sterile if package is intact

Clear

Not Made With

Natural Rubber Latex

Single Use Only

SoluPrep™ S Sterile Antiseptic Solution is a sterile

patient preoperative skin preparation. Each unit dose

applicator contains 0.36 fl oz (10.5 mL) of solution which

covers a 8.4 in. x 15.6 in. area.

3M recommends all users participate in product

in-service training prior to use. In-servicing is available

on video, from your 3M sales representative or at the 3M

website (www.3m.com).

SoluPrep™ S Sterile Antiseptic Solution is an

antimicrobial skin preparation. It is recommended that

the prep remain on the skin after the procedure for

continued protection. The prep will gradually wear away.

If however early removal is desired, use soap and water or 70% isopropyl

alcohol.

REF 67134

0.36 fl oz • 10.5 mL

Made in USA with Globally

Sourced Materials

3M Company

2510 Conway Ave.

St. Paul, MN 55144 USA

1-800-228-3957

www.3M.com/Medical

3M and SoluPrep are trademarks of 3M.

@ 2022, 3M. All rights reserved.

34-8727-1934-8

Principal Display Panel – 3M SoluPrep™ S 10.5mL Clear Applicator Pouch Label

3M

REF 67134

NDC 17518-083-02

Single

Use Only

SoluPrep™ S

chlorhexidine gluconate (2% w/v) and isopropyl alcohol (70% v/v)

Patient Preoperative Skin Preparation

for head, neck, and small prep areas

Sterile Antiseptic Solution

Applicator is sterile if package is intact

0.36 fl oz • 10.5 mL

Clear